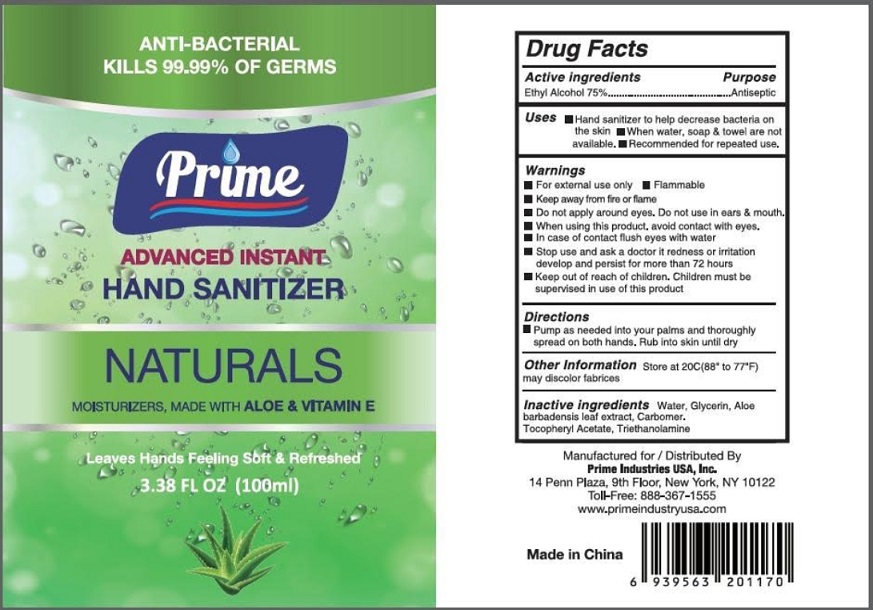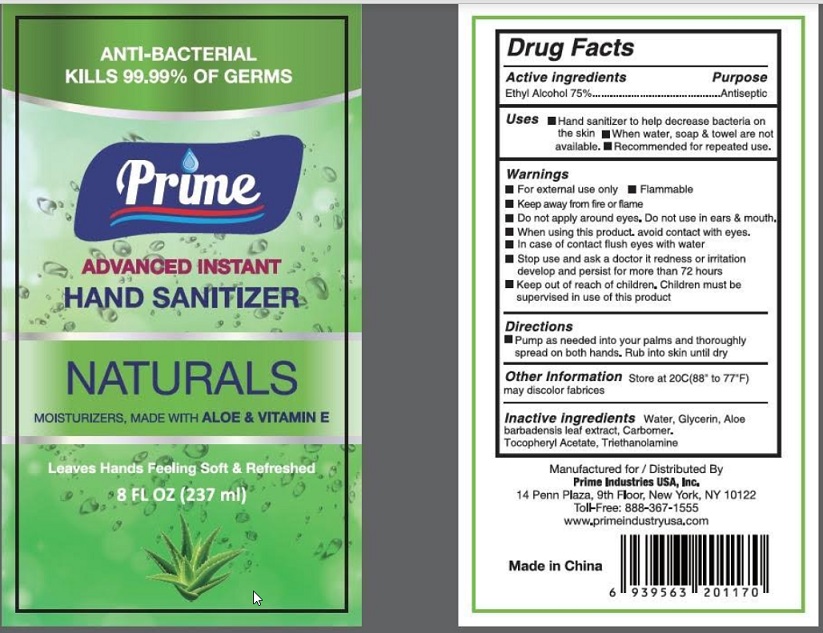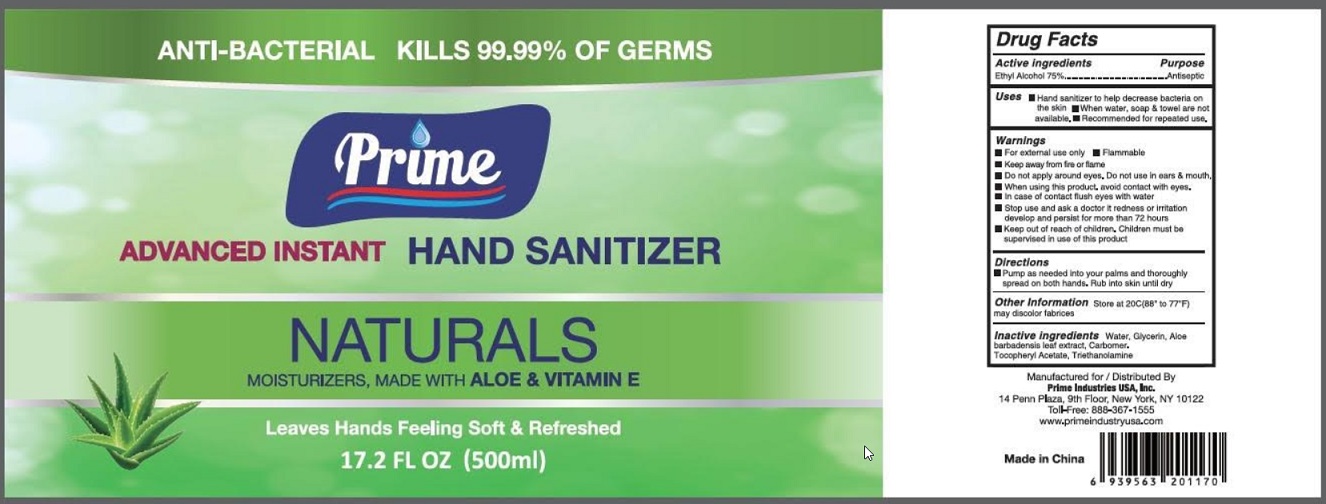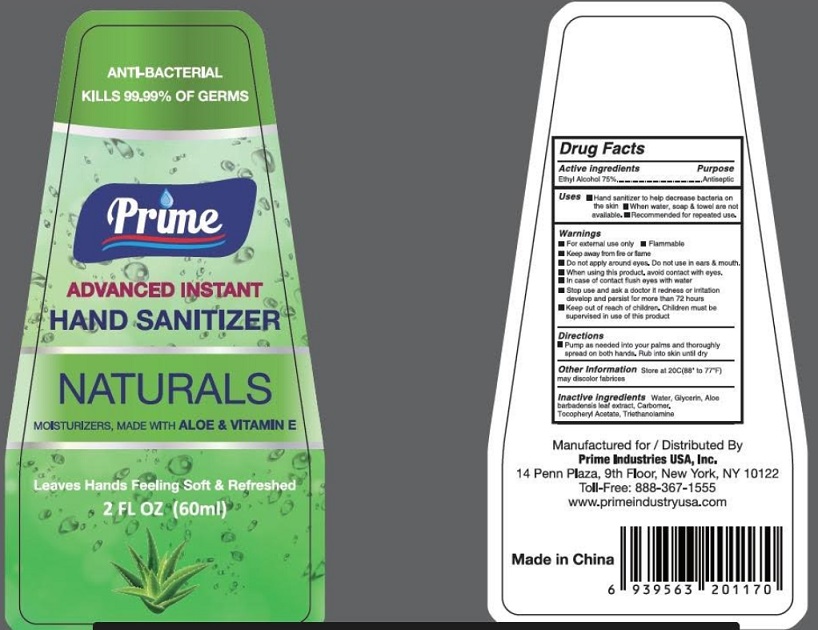 DRUG LABEL: PRIME
NDC: 79382-001 | Form: GEL
Manufacturer: Prime Industries Usa, Inc
Category: otc | Type: HUMAN OTC DRUG LABEL
Date: 20200804

ACTIVE INGREDIENTS: ALCOHOL 75 mL/100 mL
INACTIVE INGREDIENTS: WATER; GLYCERIN; ALOE VERA LEAF; CARBOMER HOMOPOLYMER, UNSPECIFIED TYPE; .ALPHA.-TOCOPHEROL ACETATE; TROLAMINE

Active Ingredient

Ethyl Alcohol 75% v/v.

Purpose

Antiseptic

Uses

- Hand sanitizer to help decrease bacteria on the skin.
- When water, soap & towel are not available.
- Recommended for repealed use.

Warnings

- For external use only
- Flammable. Keep away from fire or flame.
- Do not apply around eyes. Do not use in ears & mouth.
- When using this product avoid contact with eyes.
- In case of contact flush eyes with water.
- Stop use and ask a doctor if redness or irritation develop and persist for more than 72 hours.

Keep out of reach of children. Children must be supervised in use of this product.

Directions

- Pump as needed into your palms and thoroughly spread on both hand.
- Rub into skin until dry.

Other information

- Store at 20oC (88-77oF).
- May discolor fabrics.

Inactive ingredients

Water, Glycerin, Aloe barbadensis leaf extract, Carbomer, Tocopheryl Acetate, Triethanolamine.

Package Label - Principal Display Panel

60 mL

100 mL

237 mL

500 mL